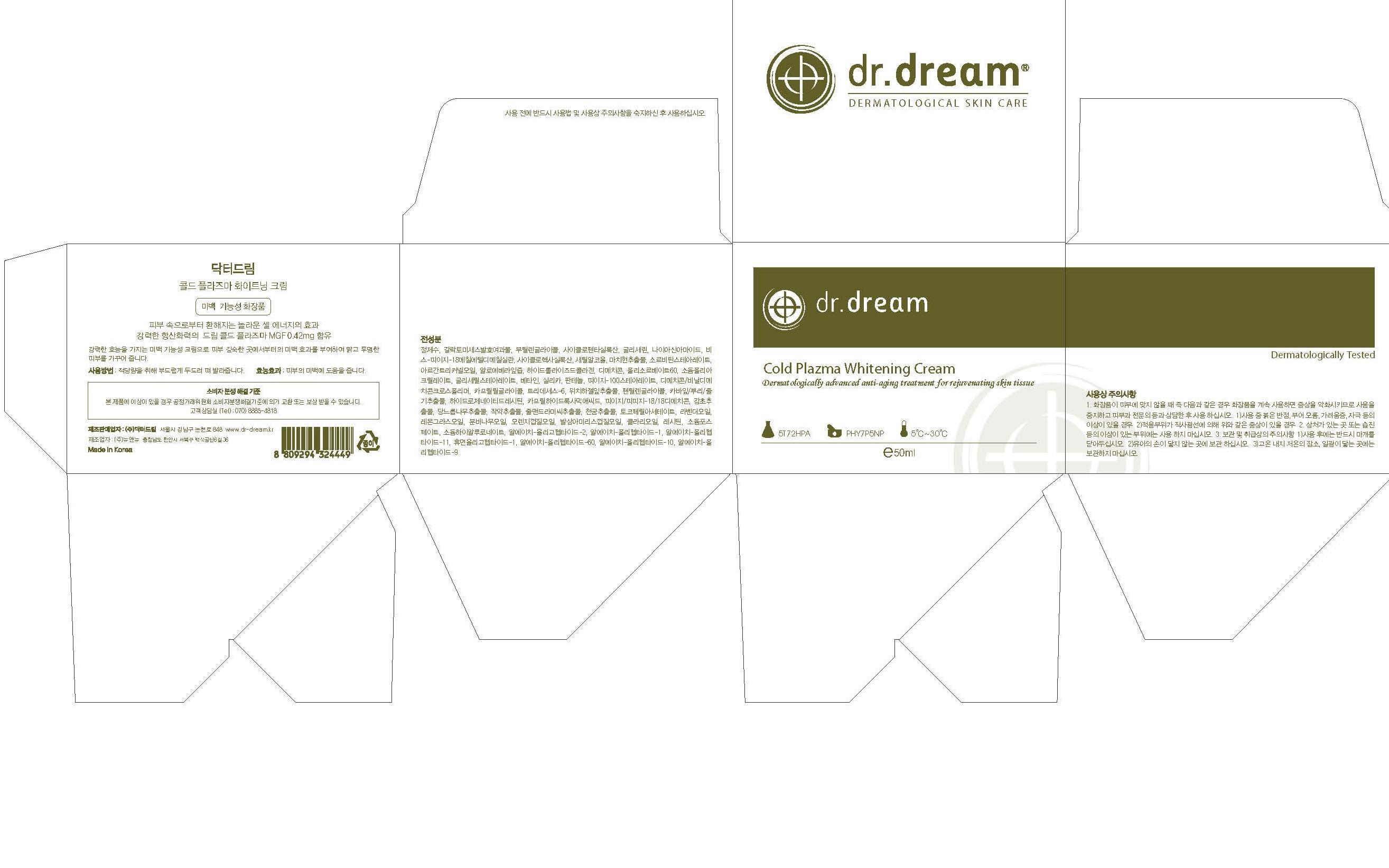 DRUG LABEL: Dr. Dream Cold Plazma Whitening
NDC: 53077-5001 | Form: CREAM
Manufacturer: Dr. Dream Inc
Category: otc | Type: HUMAN OTC DRUG LABEL
Date: 20120925

ACTIVE INGREDIENTS: WITCH HAZEL 0.1 mg/100 mL
INACTIVE INGREDIENTS: MUSA BASJOO WHOLE; ACETYL HEXAPEPTIDE-8; PALMITOYL OLIGOPEPTIDE; PALMITOYL TETRAPEPTIDE-7; POLYSORBATE 60; GLYCERIN; CAPRYLHYDROXAMIC ACID; ADENOSINE; AMMONIUM ACRYLOYLDIMETHYLTAURATE/VP COPOLYMER; NEOPENTYL GLYCOL; BLACK OLIVE; SODIUM CHONDROITIN SULFATE (PORCINE; 5500 MW); LAVANDULA ANGUSTIFOLIA FLOWERING TOP; CYMBOPOGON SCHOENANTHUS OIL; ABIES SIBIRICA LEAF OIL; ORANGE; AMYRIS BALSAMIFERA OIL; CLARY SAGE OIL; LECITHIN, SOYBEAN; SODIUM PHOSPHATE; HYALURONATE SODIUM; THIOREDOXIN; PREZATIDE COPPER; PALMITOYL PENTAPEPTIDE-4; GLYCINE; GLUTAMINE; LYSINE; LEUCINE; METHIONINE; VALINE; SERINE; CYSTEINE; CYSTINE; ASPARAGINE; ALANINE; ARGININE; ORNITHINE; ISOLEUCINE; TYROSINE; THREONINE; TRYPTOPHAN; PHENYLALANINE; PROLINE; HISTIDINE

Drug Facts

ACTIVE INGREDIENT

witch hazel

INACTIVE INGREDIENT

water, butylene glycol, glycerin, cetyl ethylhexanoate, betaine, olive fruit oil, grape seed oil, polyglyceryl-3 methylglucose distearate, cyclopentasiloxane, beewax, cetyl alcohol, anthemis nobilis flower extract, bentinite, dimethicone, neopentyl glycol diheptanoate, stearyl alcohol, argania spinosa kernel oil, caprylic/crpric triglyceride, grape seed extract, polysorbate 60, dimethicone/vinyl dimethicone crosspolymer, sorbitan stearate, glyceryl stearate, stearic acid, panthenol, peg-100 stearate, synthetic wax peg-10 dimethicone crosspolymer, caprylyl glycol, tocopheryl acetate, torreya nucifera extract, cornus kousa extract, rosa multiflora fruit extract, chloranthus glaber extract, musa basjoo extract, pentylene glycol, palmitoyl oligopeptide, adenosine, isohexadecane, polysorbate 80, disodium edta, dipotassium glycyrrhizate, lavender oil, cymbopogon schoenanthus oil, abies sibirica oil, orange peel oil, amyris balsamifera bark oil, clary oil, lecithin, sodium phosphate, copper tripeptide-1, glycine, glutamine, lysine, leucine, methionine, valine serine, cysteine, cystine, asparagine, alanine, arginine, ornithine, isoleucine, tyrosine, threonine, tryptophan, phenylalanine, proline, histidine

PURPOSE

whitening care

keep out of reach of the children

INDICATIONS AND USAGE

After applying dream Advanced Facial Treatment Serum, use the built-in spatula to take out the proper amount and apply it to your face as massaging to be well absorbed. There would be better effect if you apply it twice a day in the morning and evening.

When using this product
- keep out of eyes, ears, and mouth. If contact occurs, rinse with plenty of cold water right away and contact a physician. If swallowing, drink plenty of water and contact a physician

DOSAGE AND ADMINISTRATION

for external use only